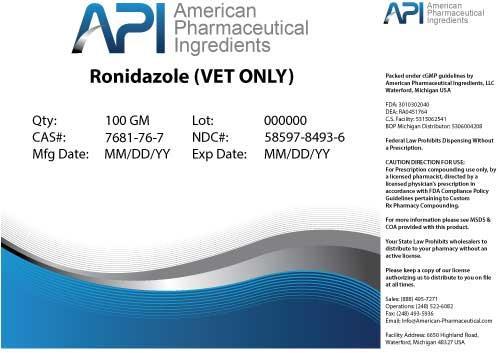 DRUG LABEL: Ronidazole
NDC: 58597-8493 | Form: POWDER
Manufacturer: AMERICAN PHARMACEUTICAL INGREDIENTS LLC
Category: other | Type: BULK INGREDIENT
Date: 20140429

ACTIVE INGREDIENTS: Ronidazole 1 g/1 g

Ronidazole